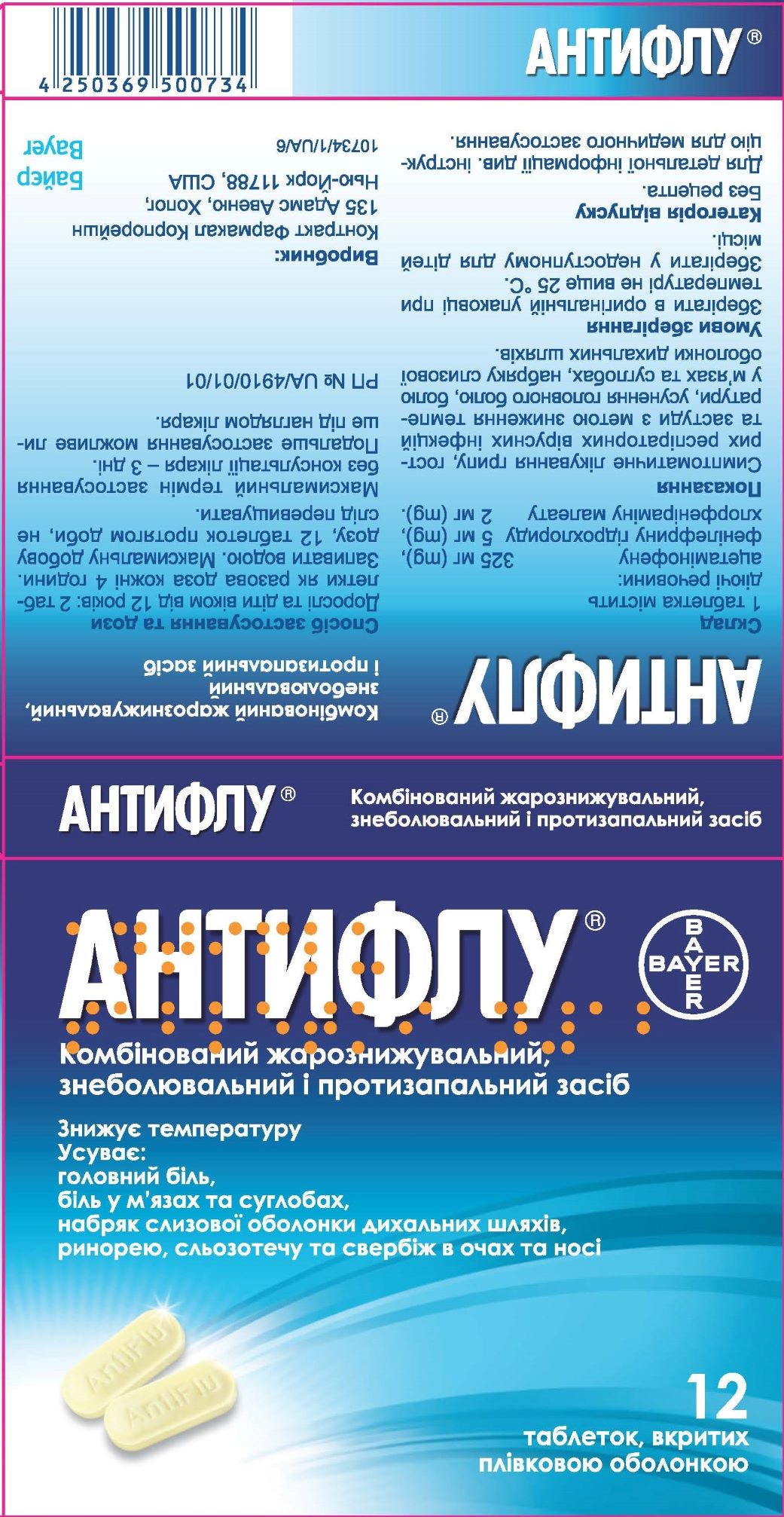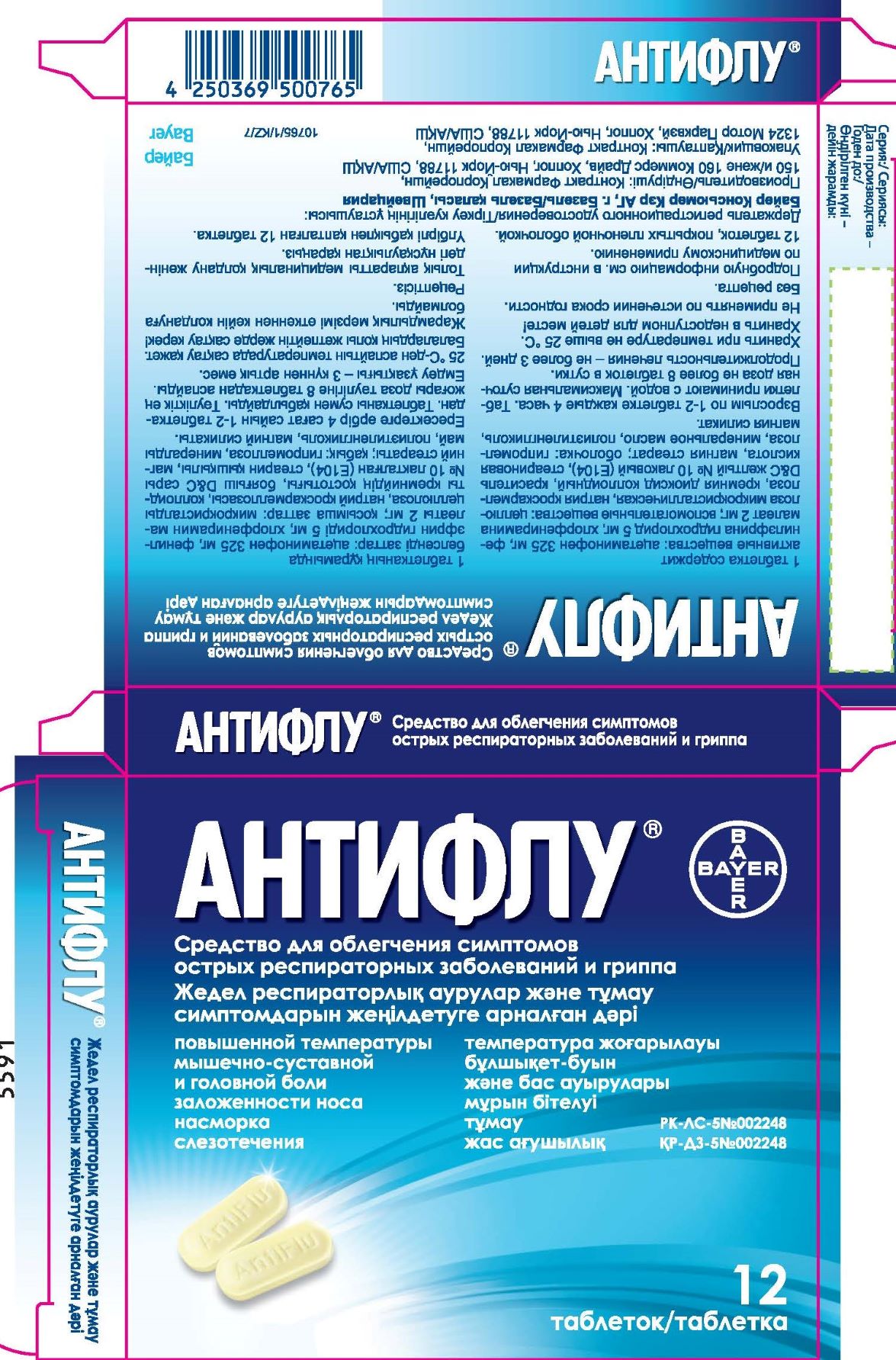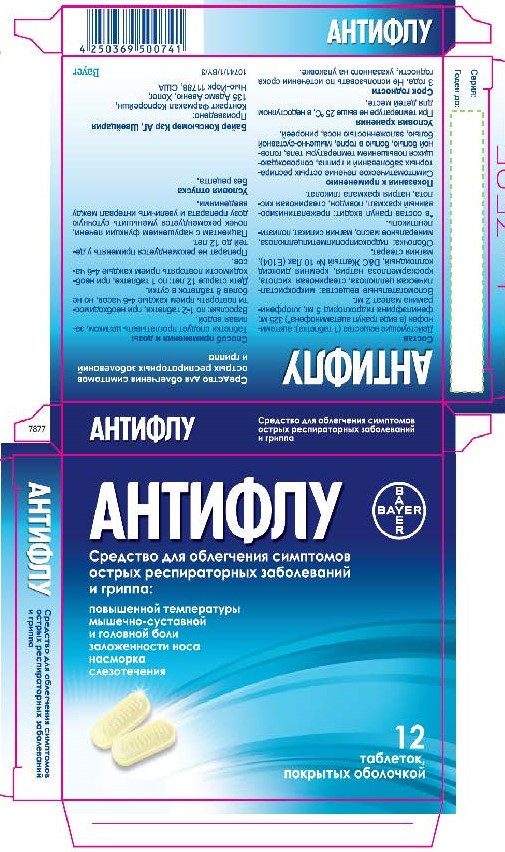 DRUG LABEL: Acetaminophen, Phenylephrine Hydrochloride, Chlorpheniramine Maleate
NDC: 10267-2634 | Form: TABLET, FILM COATED
Manufacturer: Contract Pharmacal Corp.
Category: otc | Type: HUMAN OTC DRUG LABEL
Date: 20221129

ACTIVE INGREDIENTS: ACETAMINOPHEN 325 mg/1 1; CHLORPHENIRAMINE MALEATE 2 mg/1 1; PHENYLEPHRINE HYDROCHLORIDE 5 mg/1 1
INACTIVE INGREDIENTS: D&C YELLOW NO. 10; POLYETHYLENE GLYCOL 400; STARCH, CORN; MAGNESIUM STEARATE; HYPROMELLOSES; POVIDONE K30; SILICON DIOXIDE; SODIUM STARCH GLYCOLATE TYPE A POTATO; STEARIC ACID; MICROCRYSTALLINE CELLULOSE; CROSCARMELLOSE SODIUM; TALC; LIGHT MINERAL OIL

2634 - Export